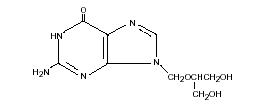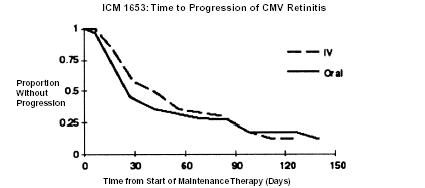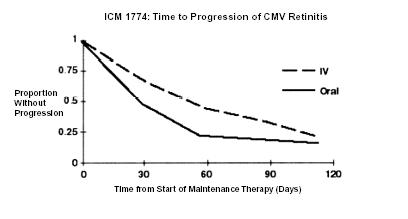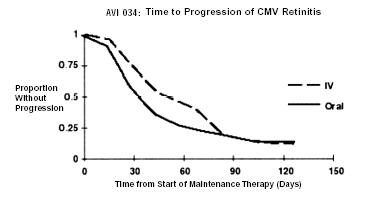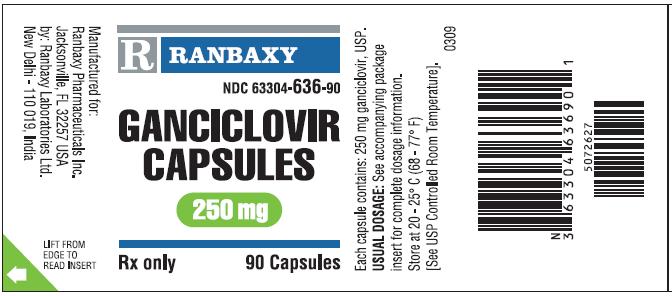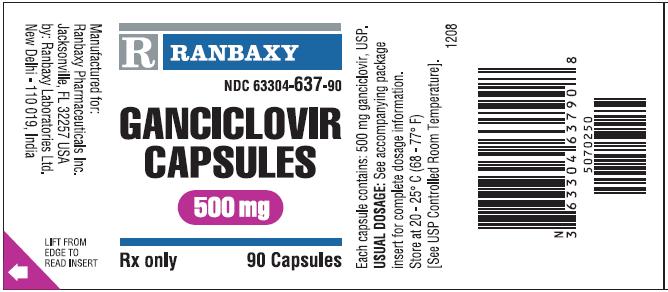 DRUG LABEL: GANCICLOVIR
NDC: 63304-636 | Form: CAPSULE
Manufacturer: Ranbaxy Pharmaceuticals Inc.
Category: prescription | Type: HUMAN PRESCRIPTION DRUG LABEL
Date: 20111020

ACTIVE INGREDIENTS: GANCICLOVIR 250 mg/1 1
INACTIVE INGREDIENTS: CROSCARMELLOSE SODIUM; FD&C BLUE NO. 2; GELATIN; FERRIC OXIDE BLACK; FERRIC OXIDE YELLOW; LECITHIN, SOYBEAN; MAGNESIUM STEARATE; CELLULOSE, MICROCRYSTALLINE; POVIDONE; SHELLAC; TITANIUM DIOXIDE

GANCICLOVIR CAPSULES
Rx only
FOR ORAL ADMINISTRATION

WARNING

THE CLINICAL TOXICITY OF GANCICLOVIR INCLUDES GRANULOCYTOPENIA, ANEMIA AND THROMBOCYTOPENIA. IN ANIMAL STUDIES GANCICLOVIR WAS CARCINOGENIC, TERATOGENIC AND CAUSED ASPERMATOGENESIS.

GANCICLOVIR CAPSULES ARE INDICATED ONLY FOR PREVENTION OF CMV DISEASE IN PATIENTS WITH ADVANCED HIV INFECTION AT RISK FOR CMV DISEASE, FOR MAINTENANCE TREATMENT OF CMV RETINITIS IN IMMUNOCOMPROMISED PATIENTS, AND FOR PREVENTION OF CMV DISEASE IN SOLID ORGAN TRANSPLANT RECIPIENTS (see INDICATIONS AND USAGE).

BECAUSE GANCICLOVIR CAPSULES ARE ASSOCIATED WITH A RISK OF MORE RAPID RATE OF CMV RETINITIS PROGRESSION, THEY SHOULD BE USED AS MAINTENANCE TREATMENT ONLY IN THOSE PATIENTS FOR WHOM THIS RISK IS BALANCED BY THE BENEFIT ASSOCIATED WITH AVOIDING DAILY INTRAVENOUS INFUSIONS.

DESCRIPTION

Ganciclovir is a synthetic guanine derivative active against cytomegalovirus (CMV).

Ganciclovir is available as 250 mg and 500 mg capsules. Each capsule contains 250 mg or 500 mg ganciclovir, USP respectively, and inactive ingredients croscarmellose sodium, FD&C blue #2, gelatin, iron oxide black, iron oxide yellow, lecithin, magnesium stearate, microcrystalline cellulose, povidone, shellac, simethicone, and titanium dioxide.

Ganciclovir is a white to off-white crystalline powder with a molecular formula of C9H13N504 and a molecular weight of 255.23. The chemical name for ganciclovir is 9-[[2-hydroxy-1-(hydroxymethyl)ethoxy]methyl]guanine. Ganciclovir is a polar hydrophilic compound with a solubility of 2.6 mg/mL in water at 25° C and an n-octanol/water partition coefficient of 0.022. The pKas for ganciclovir are 2.2 and 9.4. The molecular structure of ganciclovir is:

All doses in this insert are specified in terms of ganciclovir.

VIROLOGY

Mechanism of Action: Ganciclovir is an acyclic nucleoside analogue of 2'-deoxyguanosine that inhibits replication of herpes viruses. Ganciclovir has been shown to be active against cytomegalovirus (CMV) and herpes simplex virus (HSV) in human clinical studies.

To achieve anti-CMV activity, ganciclovir is phosphorylated first to the monophosphate form by a CMV-encoded (UL97 gene) protein kinase homologue, then to the di- and triphosphate forms by cellular kinases. Ganciclovir triphosphate concentrations may be 100-fold greater in CMV-infected than in uninfected cells, indicating preferential phosphorylation in infected cells. Ganciclovir triphosphate, once formed, persists for days in the CMV-infected cell. Ganciclovir triphosphate is believed to inhibit viral DNA synthesis by (1) competitive inhibition of viral DNA polymerases; and (2) incorporation into viral DNA, resulting in eventual termination of viral DNA elongation.

Antiviral Activity: The median concentration of ganciclovir that inhibits CMV replication (IC50) in vitro (laboratory strains or clinical isolates) has ranged from 0.02 to 3.48 mcg/mL. Ganciclovir inhibits mammalian cell proliferation (CIC50) in vitro at higher concentrations ranging from 30 to 725 mcg/mL. Bone marrow-derived colony-forming cells are more sensitive (CIC50 0.028 to 0.7 mcg/mL). The relationship of in vitro sensitivity of CMV to ganciclovir and clinical response has not been established.

Clinical Antiviral Effect of Ganciclovir Capsules:In trials comparing ganciclovir IV with ganciclovir capsules for the maintenance treatment of CMV retinitis in patients with AIDS, serial urine cultures and other available cultures (semen, biopsy specimens, blood and others) showed that a small proportion of patients remained culture-positive during maintenance therapy with no statistically significant differences in CMV isolation rates between treatment groups.

A study of ganciclovir capsules (1000 mg q8h) for prevention of CMV disease in individuals with advanced HIV infection (ICM 1654) evaluated antiviral activity as measured by CMV isolation in culture; most cultures were from urine. At baseline, 40% (176/436) and 44% (92/210) of ganciclovir and placebo recipients, respectively, had positive cultures (urine or blood). After 2 months on treatment, 10% vs 44% of ganciclovir vs placebo recipients had positive cultures.

Viral Resistance: The current working definition of CMV resistance to ganciclovir in in vitro assays is IC50 > 3 mcg/mL (12 µM). CMV resistance to ganciclovir has been observed in individuals with AIDS and CMV retinitis who have never received ganciclovir therapy. In a controlled study of oral ganciclovir for prevention of AIDS-associated CMV disease, 364 individuals had one or more cultures performed after at least 90 days of ganciclovir treatment. Of these, 113 had at least one positive culture. The last available isolate from each subject was tested for reduced sensitivity, and 2 of 40 were found to be resistant to ganciclovir. These resistant isolates were associated with subsequent treatment failure for retinitis.

The possibility of viral resistance should be considered in patients who show poor clinical response or experience persistent viral excretion during therapy. The principal mechanism of resistance to ganciclovir in CMV is the decreased ability to form the active triphosphate moiety; resistant viruses have been described that contain mutations in the UL97 gene of CMV that controls phosphorylation of ganciclovir. Mutations in the viral DNA polymerase have also been reported to confer viral resistance to ganciclovir.

CLINICAL PHARMACOLOGY

Pharmacokinetics

BECAUSE THE MAJOR ELIMINATION PATHWAY FOR GANCICLOVIR IS RENAL, DOSAGE REDUCTIONS ACCORDING TO CREATININE CLEARANCE SHOULD BE CONSIDERED FOR GANCICLOVIR CAPSULES. FOR DOSING INSTRUCTIONS IN PATIENTS WITH RENAL IMPAIRMENT, REFER TO DOSAGE AND ADMINISTRATION.

Absorption: The absolute bioavailability of oral ganciclovir under fasting conditions was approximately 5% (n = 6) and following food was 6% to 9% (n = 32). When ganciclovir was administered orally with food at a total daily dosage of 3 g/day (500 mg q3h, 6 times daily and 1000 mg tid), the steady-state absorption as measured by area under the serum concentration vs time curve (AUC) over 24 hours and maximum serum concentrations (Cmax) were similar following both regimens with an AUC0-24 of 15.9 ± 4.2 (mean ± SD) and 15.4 ± 4.3 mcg•hr/mL and Cmax of 1.02 ± 0.24 and 1.18 ± 0.36 mcg/mL, respectively (n = 16).

Food Effects: When ganciclovir capsules were given with a meal containing 602 calories and 46.5% fat at a dosage of 1000 mg every 8 hours to 20 HIV-positive subjects, the steady-state AUC increased by 22 ± 22% (range: -6% to 68%) and there was a significant prolongation of time to peak serum concentrations (Tmax) from 1.8 ± 0.8 to 3 ± 0.6 hours and a higher Cmax (0.85 ± 0.25 vs 0.96 ± 0.27 mcg/mL) (n = 20).

Distribution: For ganciclovir capsules, no correlation was observed between AUC and reciprocal weight (range: 55 to 128 kg); oral dosing according to weight is not required. Binding to plasma proteins was 1% to 2% over ganciclovir concentrations of 0.5 and 51 mcg/mL.

Metabolism: Following oral administration of a single 1000 mg dose of ^14C-labeled ganciclovir, 86 ± 3% of the administered dose was recovered in the feces and 5 ± 1% was recovered in the urine (n = 4). No metabolite accounted for more than 1% to 2% of the radioactivity recovered in urine or feces.

Elimination: When administered orally, it exhibits linear kinetics up to a total daily dose of 4 g/day. Renal excretion of unchanged drug by glomerular filtration and active tubular secretion is the major route of elimination of ganciclovir. After oral administration of ganciclovir, steady-state is achieved within 24 hours. Renal clearance following oral administration was 3.1 ± 1.2 mL/min/kg (n = 22). Half-life was 4.8 ± 0.9 hours (n = 39) following oral administration.

Special Populations: The pharmacokinetics of ganciclovir following oral administration of ganciclovir capsules were evaluated in 44 patients, who were either solid organ transplant recipients or HIV positive. Apparent oral clearance of ganciclovir decreased and AUC0-24h increased with diminishing renal function (as expressed by creatinine clearance).

Based on these observations, it is necessary to modify the dosage of ganciclovir in patients with renal impairment (see DOSAGE AND ADMINISTRATION).

Hemodialysis reduces plasma concentrations of ganciclovir by about 50% after oral administration.

Race/Ethnicity and Gender: The effects of race/ethnicity and gender were studied in subjects receiving a dose regimen of 1000 mg every 8 hours. Although the numbers of blacks (16%) and Hispanics (20%) were small, there appeared to be a trend towards a lower steady-state Cmax and AUC0-8 in these subpopulations as compared to Caucasians. No definitive conclusions regarding gender differences could be made because of the small number of females (12%); however, no differences between males and females were observed.

Elderly: No studies have been conducted in adults older than 65 years of age.

INDICATIONS AND USAGE

Ganciclovir capsules are indicated for the prevention of CMV disease in solid organ transplant recipients and in individuals with advanced HIV infection at risk for developing CMV disease. Ganciclovir capsules are also indicated as an alternative to the intravenous formulation for maintenance treatment of CMV retinitis in immunocompromised patients, including patients with AIDS, in whom retinitis is stable following appropriate induction therapy and for whom the risk of more rapid progression is balanced by the benefit associated with avoiding daily IV infusions (see CLINICAL TRIALS).

SAFETY AND EFFICACY OF GANCICLOVIR HAVE NOT BEEN ESTABLISHED FOR CONGENITAL OR NEONATAL CMV DISEASE; NOT FOR THE TREATMENT OF ESTABLISHED CMV DISEASE OTHER THAN RETINITIS; NOR FOR USE IN NON-IMMUNOCOMPROMISED INDIVIDUALS. THE SAFETY AND EFFICACY OF GANCICLOVIR CAPSULES HAVE NOT BEEN ESTABLISHED FOR TREATING ANY MANIFESTATION OF CMV DISEASE OTHER THAN MAINTENANCE TREATMENT OF CMV RETINITIS.

CLINICAL TRIALS

1. Treatment of CMV Retinitis

The diagnosis of CMV retinitis should be made by indirect ophthalmoscopy. Other conditions in the differential diagnosis of CMV retinitis include candidiasis, toxoplasmosis, histoplasmosis, retinal scars and cotton wool spots, any of which may produce a retinal appearance similar to CMV. For this reason it is essential that the diagnosis of CMV be established by an ophthalmologist familiar with the retinal presentation of these conditions. The diagnosis of CMV retinitis may be supported by culture of CMV from urine, blood, throat or other sites, but a negative CMV culture does not rule out CMV retinitis.

Studies Comparing Ganciclovir-Capsules to Ganciclovir-IV:

Population Characteristics in Studies ICM 1653, ICM 1774 and AVI 034

 |  | ICM 1653 (n = 121) | ICM 1774 (n = 225) | AVI 034 (n = 159)
Median age (years) Range |  | 38 | 37 | 39
Median age (years) Range |  | 24 to 62 | 22 to 56 | 23 to 62
Sex | Males | 116 (96%) | 222 (99%) | 148 (93%)
Sex | Female | 5 (4%) | 3 (1%) | 10 (6%)
Ethnicity | Asian | 3 (3%) | 5 (2%) | 7 (4%)
Ethnicity | Black | 11 (9%) | 9 (4%) | 3 (2%)
Ethnicity | Caucasian | 98 (81%) | 186 (83%) | 140 (88%)
Ethnicity | Other | 9 (7%) | 25 (11%) | 8 (5%)
Median CD4 Count Range |  | 9.5 | 7 | 10
Median CD4 Count Range |  | 0 to 141 | 0 to 80 | 0 to 320
Mean (SD) Observation Time (days) |  | 107.9 (43) | 97.6 (42.5) | 80.9 (47)

ICM 1653: In this randomized, open-label, parallel group trial, conducted between March 1991 and November 1992, patients with AIDS and newly diagnosed CMV retinitis received a 3-week induction course of ganciclovir- IV solution, 5 mg/kg bid for 14 days followed by 5 mg/kg once daily for 1 additional week.^1 Following the 21-day intravenous induction course, patients with stable CMV retinitis were randomized to receive 20 weeks of maintenance treatment with either ganciclovir-IV solution, 5 mg/kg once daily, or ganciclovir capsules, 500 mg 6 times daily (3000 mg/day). The study showed that the mean [95% CI] and median [95% CI] times to progression of CMV retinitis, as assessed by masked reading of fundus photographs, were 57 days [44, 70] and 29 days [28, 43], respectively, for patients on oral therapy compared to 62 days [50, 73] and 49 days [29, 61], respectively, for patients on intravenous therapy. The difference [95% CI] in the mean time to progression between the oral and intravenous therapies (oral - IV) was -5 days [-22, 12]. See Figure 1 for comparison of the proportion of patients remaining free of progression over time.

ICM 1774: In this three-arm, randomized, open-label, parallel group trial, conducted between June 1991 and August 1993, patients with AIDS and stable CMV retinitis following from 4 weeks to 4 months of treatment with ganciclovir-IV solution were randomized to receive maintenance treatment with ganciclovir-IV solution, 5 mg/kg once daily, ganciclovir capsules, 500 mg 6 times daily, or ganciclovir capsules, 1000 mg tid for 20 weeks. The study showed that the mean [95% CI] and median [95% CI] times to progression of CMV retinitis, as assessed by masked reading of fundus photographs, were 54 days [48, 60] and 42 days [31, 54], respectively, for patients on oral therapy compared to 66 days [56, 76] and 54 days [41, 69], respectively, for patients on intravenous therapy. The difference [95% CI] in the mean time to progression between the oral and intravenous therapies (oral - IV) was -12 days [-24, 0]. See Figure 2 for comparison of the proportion of patients remaining free of progression over time.

AVI 034: In this randomized, open-label, parallel group trial, conducted between June 1991 and February 1993, patients with AIDS and newly diagnosed (81%) or previously treated (19%) CMV retinitis who had tolerated 10 to 21 days of induction treatment with ganciclovir-IV, 5 mg/kg twice daily, were randomized to receive 20 weeks of maintenance treatment with either ganciclovir capsules, 500 mg 6 times daily or ganciclovir-IV solution, 5 mg/kg/day.^2 The mean [95% CI] and median [95% CI] times to progression of CMV retinitis, as assessed by masked reading of fundus photographs, were 51 days [44, 57] and 41 days [31, 45], respectively, for patients on oral therapy compared to 62 days [52, 72] and 60 days [42, 83], respectively, for patients on intravenous therapy. The difference [95% CI] in the mean time to progression between the oral and intravenous therapies (oral - IV) was -11 days [-24, 1]. See Figure 3 for comparison of the proportion of patients remaining free of progression over time.

Comparison of other CMV retinitis outcomes between oral and IV formulations (development of bilateral retinitis, progression into Zone 1, and deterioration of visual acuity), while not definitive, showed no marked differences between treatment groups in these studies. Because of low event rates among these endpoints, these studies are underpowered to rule out significant differences in these endpoints.

Figure 1 - ICM 1653

Figure 2 - ICM 1774

Figure 3 - AVI 034

2. Prevention of CMV Disease in Subjects With AIDS

ICM 1654: In a double-blind study conducted between November 1992 and July 1994, 725 subjects with AIDS, who were CMV seropositive and/or culture positive, were randomized to receive ganciclovir capsules, 1000 mg, every 8 hours, or placebo.^3 The study population had a median age of 38 years (range: 21 to 69); were 99% male; were 82% Caucasian, 10% Hispanic, 7% African-American and 1% Asian; and had a median CD4 count of 21 (range: 0 to 100). The mean observation time was 351 days (range: 5 to 621). As shown in the following table, significantly more placebo recipients developed CMV disease.

Incidence of CMV Disease at 6, 12 and 18 Months After Enrollment (Kaplan-Meier Estimates)

 | Incidence (Number Still at Risk)
 | CMV Disease
 | Ganciclovir | Placebo
6 months | 8% (397) | 11% (190)
12 months | 14% (225) | 26% (92)
18 months | 20% (27) | 39% (9)

3. Prevention of CMV Disease in Transplant Recipients

GAN040: Ganciclovir capsules were evaluated in a randomized, double-blind, placebo-controlled study of 304 orthotopic liver transplant recipients who were CMV seropositive or recipients of an organ from a seropositive donor. Administration of ganciclovir capsules (1000 mg three times daily) or matching placebo commenced as soon as patients were able to take medication by mouth, but no later than 10 days following transplantation, and continued through 14 weeks after transplantation. Dosing was adjusted for patients with an estimated creatinine clearance < 50 mL/min. The incidence of CMV disease at 6 months is summarized in the table below:

Incidence of CMV Disease at 6 Months (Kaplan-Meier Estimates)

CMV Disease at 6 months
 | Ganciclovir (n = 150) | Placebo (n = 154) | Relative Risk (95% Cl)
CMV Disease,* N (%) | 7 (4.8%) | 29 (18.9%) | 0.22 (0.10, 0.51)
CMV syndrome# | 6 (4.1%) | 19 (12.4%)
CMV hepatitis | 1 (0.7%) | 9 (5.9%)
CMV GI disease | 0 (0%) | 3 (2%)
CMV lung disease | 0 (0%) | 4 (2.6%)

* One or more CMV endpoints

# CMV syndrome: CMV viremia and unexplained fever, accompanied by malaise and/or neutropenia.

Ganciclovir capsules significantly reduced the 6-month incidence of CMV disease in patients at increased risk of CMV disease, including seronegative recipients of organs from seropositive donors (15% [3/21] with ganciclovir capsules vs 44% [11/25] with placebo), and patients receiving antilymphocyte antibodies (5% [2/44] with ganciclovir capsules vs 33% [12/37] with placebo). The incidence of HSV infection at 6 months was 4% (5/150) in ganciclovir vs 24% (36/154) in placebo recipients (relative risk: 0.13; 95% CI: 0.05, 0.32).

CONTRAINDICATIONS

Ganciclovir is contraindicated in patients with hypersensitivity to ganciclovir or acyclovir.

WARNINGS

Hematologic: Ganciclovir should not be administered if the absolute neutrophil count is less than 500 cells/µ L or the platelet count is less than 25,000 cells/µ L. Granulocytopenia (neutropenia), anemia and thrombocytopenia have been observed in patients treated with ganciclovir. The frequency and severity of these events vary widely in different patient populations (see ADVERSE EVENTS).

Ganciclovir should, therefore, be used with caution in patients with pre-existing cytopenias or with a history of cytopenic reactions to other drugs, chemicals or irradiation. Granulocytopenia usually occurs during the first or second week of treatment but may occur at any time during treatment. Cell counts usually begin to recover within 3 to 7 days of discontinuing drug.

Impairment of Fertility: Animal data indicate that administration of ganciclovir causes inhibition of spermatogenesis and subsequent infertility. These effects were reversible at lower doses and irreversible at higher doses (see PRECAUTIONS: Carcinogenesis, Mutagenesis and Impairment of Fertility). Although data in humans have not been obtained regarding this effect, it is considered probable that ganciclovir at the recommended doses causes temporary or permanent inhibition of spermatogenesis. Animal data also indicate that suppression of fertility in females may occur.

Teratogenesis: Because of the mutagenic and teratogenic potential of ganciclovir, women of childbearing potential should be advised to use effective contraception during treatment. Similarly, men should be advised to practice barrier contraception during and for at least 90 days following treatment with ganciclovir (see Pregnancy; Teratogenic Effects: Category C).

PRECAUTIONS

General

Since ganciclovir is excreted by the kidneys, normal clearance depends on adequate renal function. IF RENAL FUNCTION IS IMPAIRED, DOSAGE ADJUSTMENTS SHOULD BE CONSIDERED FOR GANCICLOVIR CAPSULES. Such adjustments should be based on measured or estimated creatinine clearance values (see DOSAGE AND ADMINISTRATION).

Information for Patients

All patients should be informed that the major toxicities of ganciclovir are granulocytopenia (neutropenia), anemia and thrombocytopenia and that dose modifications may be required, including discontinuation. The importance of close monitoring of blood counts while on therapy should be emphasized. Patients should be informed that ganciclovir has been associated with elevations in serum creatinine.

Patients should be instructed to take ganciclovir capsules with food to maximize bioavailability.

Patients should be advised that ganciclovir has caused decreased sperm production in animals and may cause infertility in humans. Women of childbearing potential should be advised that ganciclovir causes birth defects in animals and should not be used during pregnancy. Women of childbearing potential should be advised to use effective contraception during treatment with ganciclovir. Similarly, men should be advised to practice barrier contraception during and for at least 90 days following treatment with ganciclovir.

Patients should be advised that ganciclovir causes tumors in animals. Although there is no information from human studies, ganciclovir should be considered a potential carcinogen.

All HIV+ Patients: These patients may be receiving zidovudine (Retrovir®*). Patients should be counseled that treatment with both ganciclovir and zidovudine simultaneously may not be tolerated by some patients and may result in severe granulocytopenia (neutropenia). Patients with AIDS may be receiving didanosine (Videx®#). Patients should be counseled that concomitant treatment with both ganciclovir and didanosine can cause didanosine serum concentrations to be significantly increased.

HIV+ Patients With CMV Retinitis: Ganciclovir is not a cure for CMV retinitis, and immunocompromised patients may continue to experience progression of retinitis during or following treatment. Patients should be advised to have ophthalmologic follow-up examinations at a minimum of every 4 to 6 weeks while being treated with ganciclovir. Some patients will require more frequent follow-up.

Laboratory Testing

Due to the frequency of neutropenia, anemia and thrombocytopenia in patients receiving ganciclovir (see ADVERSE EVENTS), it is recommended that complete blood counts and platelet counts be performed frequently, especially in patients in whom ganciclovir or other nucleoside analogues have previously resulted in leukopenia, or in whom neutrophil counts are less than 1000 cells/µL at the beginning of treatment. Increased serum creatinine levels have been observed in trials evaluating ganciclovir. Patients should have serum creatinine or creatinine clearance values monitored carefully to allow for dosage adjustments in renally impaired patients (see DOSAGE AND ADMINISTRATION).

Drug Interactions

Didanosine: At an oral dose of 1000 mg of ganciclovir every 8 hours and didanosine, 200 mg every 12 hours, the steady-state didanosine AUC0-12 increased 111 ± 114% (range: 10% to 493%) when didanosine was administered either 2 hours prior to or concurrent with administration of ganciclovir (n = 12 patients, 23 observations). A decrease in steady-state ganciclovir AUC of 21 ± 17% (range: -44% to 5%) was observed when didanosine was administered 2 hours prior to administration of ganciclovir, but ganciclovir AUC was not affected by the presence of didanosine when the two drugs were administered simultaneously (n = 12). There were no significant changes in renal clearance for either drug.

Zidovudine: At an oral dose of 1000 mg of ganciclovir every 8 hours, mean steady-state ganciclovir AUC0-8 decreased 17 ± 25% (range: -52% to 23%) in the presence of zidovudine, 100 mg every 4 hours (n = 12). Steady-state zidovudine AUC0-4 increased 19 ± 27% (range: -11% to 74%) in the presence of ganciclovir.

Since both zidovudine and ganciclovir have the potential to cause neutropenia and anemia, some patients may not tolerate concomitant therapy with these drugs at full dosage.

Probenecid: At an oral dose of 1000 mg of ganciclovir every 8 hours (n = 10), ganciclovir AUC0-8 increased 53 ± 91% (range: -14% to 299%) in the presence of probenecid, 500 mg every 6 hours. Renal clearance of ganciclovir decreased 22 ± 20% (range: -54% to -4%), which is consistent with an interaction involving competition for renal tubular secretion.

Imipenem-cilastatin: Generalized seizures have been reported in patients who received ganciclovir and imipenem-cilastatin. These drugs should not be used concomitantly unless the potential benefits outweigh the risks.

Other Medications: It is possible that drugs that inhibit replication of rapidly dividing cell populations such as bone marrow, spermatogonia and germinal layers of skin and gastrointestinal mucosa may have additive toxicity when administered concomitantly with ganciclovir. Therefore, drugs such as dapsone, pentamidine, flucytosine, vincristine, vinblastine, adriamycin, amphotericin B, trimethoprim/sulfamethoxazole combinations or other nucleoside analogues, should be considered for concomitant use with ganciclovir only if the potential benefits are judged to outweigh the risks.

No formal drug interaction studies of ganciclovir and drugs commonly used in transplant recipients have been conducted.

Carcinogenesis, Mutagenesis T

Ganciclovir was carcinogenic in the mouse at oral doses of 20 and 1000 mg/kg/day (approximately 0.1x and 1.4x, respectively, the mean drug exposure in humans following the recommended intravenous dose of 5 mg/kg, based on area under the plasma concentration curve [AUC] comparisons). At the dose of 1000 mg/kg/day there was a significant increase in the incidence of tumors of the preputial gland in males, forestomach (nonglandular mucosa) in males and females, and reproductive tissues (ovaries, uterus, mammary gland, clitoral gland and vagina) and liver in females. At the dose of 20 mg/kg/day, a slightly increased incidence of tumors was noted in the preputial and harderian glands in males, forestomach in males and females, and liver in females. No carcinogenic effect was observed in mice administered ganciclovir at 1 mg/kg/day (estimated as 0.01x the human dose based on AUC comparison). Except for histiocytic sarcoma of the liver, ganciclovir- induced tumors were generally of epithelial or vascular origin. Although the preputial and clitoral glands, forestomach and harderian glands of mice do not have human counterparts, ganciclovir should be considered a potential carcinogen in humans.

Ganciclovir increased mutations in mouse lymphoma cells and DNA damage in human lymphocytes in vitro at concentrations between 50 to 500 and 250 to 2000 mcg/mL, respectively. Ganciclovir was not mutagenic in the Ames Salmonella assay at concentrations of 500 to 5000 mcg/mL.

Impairment of Fertility T

Ganciclovir caused decreased fertility in male mice and hypospermatogenesis in mice and dogs following daily administration of doses ranging from 0.2 to 10 mg/kg.

Pregnancy: Teratogenic Effects: Pregnancy Category CT

Ganciclovir has been shown to be embryotoxic in rabbits, mice and teratogenic in rabbits. Fetal resorptions were present in at least 85% of rabbits and mice administered 60 mg/kg/day and 108 mg/kg/day (2 x the human exposure based on AUC comparisons), respectively.

Effects observed in rabbits included: fetal growth retardation, embryolethality, teratogenicity and/or maternal toxicity. Teratogenic changes included cleft palate, anophthalmia/microphthalmia, aplastic organs (kidney and pancreas), hydrocephaly and brachygnathia. In mice, effects observed were maternal/fetal toxicity and embryolethality.

Ganciclovir may be teratogenic or embryotoxic at dose levels recommended for human use. There are no adequate and well-controlled studies in pregnant women. Ganciclovir should be used during pregnancy only if the potential benefits justify the potential risk to the fetus.

TFootnote: Compared with the single 5 mg/kg intravenous infusion, human exposure is doubled during the intravenous induction phase (5 mg/kg bid) and approximately halved during maintenance treatment with ganciclovir capsules (1000 mg tid). The cross-species dosage treatment should be multiplied by 2 for ganciclovir capsules.

Nursing Mothers

It is not known whether ganciclovir is excreted in human milk. However, many drugs are excreted in human milk and, because carcinogenic and teratogenic effects occurred in animals treated with ganciclovir, the possibility of serious adverse reactions from ganciclovir in nursing infants is considered likely (see Pregnancy: Teratogenic Effects: Pregnancy Category C). Mothers should be instructed to discontinue nursing if they are receiving ganciclovir. The minimum interval before nursing can safely be resumed after the last dose of ganciclovir is unknown.

Pediatric Use

SAFETY AND EFFICACY OF GANCICLOVIR IN PEDIATRIC PATIENTS HAVE NOT BEEN ESTABLISHED. THE USE OF GANCICLOVIR IN THE PEDIATRIC POPULATION WARRANTS EXTREME CAUTION DUE TO THE PROBABILITY OF LONG-TERM CARCINOGENICITY AND REPRODUCTIVE TOXICITY. ADMINISTRATION TO PEDIATRIC PATIENTS SHOULD BE UNDERTAKEN ONLY AFTER CAREFUL EVALUATION AND ONLY IF THE POTENTIAL BENEFITS OF TREATMENT OUTWEIGH THE RISKS.

Ganciclovir capsules have not been studied in pediatric patients under age 13.

Geriatric Use

The pharmacokinetic profiles of ganciclovir in elderly patients have not been established. Since elderly individuals frequently have a reduced glomerular filtration rate, particular attention should be paid to assessing renal function before and during administration of ganciclovir (see DOSAGE AND ADMINISTRATION).

Clinical studies of ganciclovir did not include sufficient numbers of subjects aged 65 and over to determine whether they respond differently from younger subjects. In general, dose selection for an elderly patient should be cautious, reflecting the greater frequency of decreased hepatic, renal, or cardiac function, and of concomitant disease or other drug therapy. Ganciclovir is known to be substantially excreted by the kidney, and the risk of toxic reactions to this drug may be greater in patients with impaired renal function. Because elderly patients are more likely to have decreased renal function, care should be taken in dose selection. In addition, renal function should be monitored and dosage adjustments should be made accordingly (see Use in Patients With Renal Impairmentand DOSAGE AND ADMINISTRATION)

Use in Patients With Renal Impairment

Ganciclovir should be used with caution in patients with impaired renal function because the half-life and plasma/serum concentrations of ganciclovir will be increased due to reduced renal clearance (see DOSAGE AND ADMINISTRATION and ADVERSE EVENTS: Renal Toxicity).

Hemodialysis has been shown to reduce plasma levels of ganciclovir by approximately 50%.

ADVERSE REACTIONS

Adverse events that occurred during clinical trials of ganciclovir capsules are summarized below, according to the participating study subject population.

Subjects With AIDS

Three controlled, randomized, phase 3 trials comparing ganciclovir-IV and ganciclovir capsules for maintenance treatment of CMV retinitis have been completed. During these trials, ganciclovir-IV or ganciclovir capsules were prematurely discontinued in 9% of subjects because of adverse events. In a placebo-controlled, randomized, phase 3 trial of ganciclovir capsules for prevention of CMV disease in AIDS, treatment was prematurely discontinued because of adverse events, new or worsening intercurrent illness, or laboratory abnormalities in 19.5% of subjects treated with ganciclovir capsules and 16% of subjects receiving placebo. Laboratory data and adverse events reported during the conduct of these controlled trials are summarized below.

Laboratory Data:

Selected Laboratory Abnormalities in Trials for Treatment of CMV Retinitis and Prevention of CMV Disease

 | CMV Retinitis Treatment* |  | CMV Disease Prevention$
Treatment | Ganciclovir Capsules# 3000 mg/day | Ganciclovir-IV## 5 mg/kg/day | Ganciclovir Capsules|| 3000 mg/day | Placebo&
Subjects, number | 320 | 175 | 478 | 234
Neutropenia:
< 500 ANC/µL | 18% | 25% | 10% | 6%
500 < 749 | 17% | 14% | 16% | 7%
750 < 1000 | 19% | 26% | 22% | 16%
Anemia:
Hemoglobin:
< 6.5 g/dL | 2% | 5% | 1% | < 1%
6.5 < 8 | 10% | 16% | 5% | 3%
8 < 9.5 | 25% | 26% | 15% | 16%
Maximum Serum Creatinine:
≥ 2.5 mg/dL | 1% | 2% | 1% | 2%
≥ 1.5 to < 2.5 | 12% | 14% | 19% | 11%
* Pooled data from Treatment Studies, ICM 1653, Study ICM 1774 and Study AVI 034.
# Mean time on therapy = 91days, including allowed reinduction treatment periods
## Mean time on therapy = 103 days, including allowed reinduction treatment periods
$ Data from Prevention Study, ICM 1654
|| Mean time on ganciclovir = 269 days
& Mean time on placebo = 240 days
(See discussion of clinical trials under INDICATIONS AND USAGE.)

Adverse events: The following table shows selected adverse events reported in 5% or more of the subjects in three controlled clinical trials during treatment with ganciclovir capsules (3000 mg/day) and in one controlled clinical trial in which ganciclovir capsules (3000 mg/day) were compared to placebo for the prevention of CMV disease.

Selected Adverse Events Reported in ≥ 5% of Subjects in Three Randomized Phase 3 Studies Comparing Ganciclovir Capsules to Ganciclovir-IV Solution for Maintenance Treatment of CMV Retinitis and in One Phase 3 Randomized Study Comparing Ganciclovir Capsules to Placebo for Prevention of CMV Disease
 |  | Maintenance Treatment Studies |  | Prevention Study
Body System | Adverse Event | Capsules (n = 326) | IV (n = 179) | Capsules (n = 478) | Placebo (n = 234)
Body as a Whole | Fever | 38% | 48% | 35% | 33%
Body as a Whole | Infection | 9% | 13% | 8% | 4%
Body as a Whole | Chills | 7% | 10% | 7% | 4%
Body as a Whole | Sepsis | 4% | 15% | 3% | 2%
Digestive System | Diarrhea | 41% | 44% | 48% | 42%
Digestive System | Anorexia | 15% | 14% | 19% | 16%
Digestive System | Vomiting | 13% | 13% | 14% | 11%
Hemic and Lymphatic System | Leukopenia | 29% | 41% | 17% | 9%
Hemic and Lymphatic System | Anemia | 19% | 25% | 9% | 7%
Hemic and Lymphatic System | Thrombocytopenia | 6% | 6% | 3% | 1%
Nervous System | Neuropathy | 8% | 9% | 21% | 15%
Other | Sweating | 11% | 12% | 14% | 12%
Other | Pruritus | 6% | 6% | 10% | 9%
Catheter Related* | Total Catheter Events | 6% | 22% | – | –
Catheter Related* | Catheter Infection | 4% | 9% | – | –
Catheter Related* | Catheter Sepsis | 1% | 8% | – | –
*Some of these events also appear under other body systems.

The following events were frequently observed in clinical trials but occurred with equal or greater frequency in placebo-treated subjects: abdominal pain, nausea, flatulence, pneumonia, paresthesia, rash.

Retinal Detachment: Retinal detachment has been observed in subjects with CMV retinitis both before and after initiation of therapy with ganciclovir. Its relationship to therapy with ganciclovir is unknown. Retinal detachment occurred in 8% of patients treated with ganciclovir capsules. Patients with CMV retinitis should have frequent ophthalmologic evaluations to monitor the status of their retinitis and to detect any other retinal pathology.

Transplant Recipients

There has been one controlled clinical trial of ganciclovir capsules for the prevention of CMV disease in transplant recipients. Laboratory data and adverse events reported during these trials are summarized below.

Laboratory Data: The following table shows the frequency of granulocytopenia (neutropenia) and thrombocytopenia observed:

Ganciclovir Capsules
 | Liver Allograft##
 | Ganciclovir Capsules (n = 150) | Placebo (n = 154)
Neutropenia
Minimum ANC
< 500/µL | 3% | 1%
Minimum ANC
500 to 1000/µL | 3% | 2%
TOTAL ANC ≤ 1000/µL | 6% | 3%
Thrombocytopenia
Platelet count < 25,000/µL | 0% | 3%
Platelet count 25,000 to 50,000/µL | 5% | 3%
TOTAL Platelet
≤ 50,000/µL | 5% | 6%
## Study GAN040. Mean duration of ganciclovir treatment = 82 days
(See discussion of clinical trails under INDICATIONS AND USAGE.)

The following table shows the frequency of elevated serum creatinine values in these controlled clinical trials:

Controlled Trials – Transplant Recipients
Ganciclovir Capsules
 | Liver Allograft Study 040
Maximum Serum Creatinine Levels | Liver Allograft Study 040
Maximum Serum Creatinine Levels | Ganciclovir Capsules (n = 150) | Placebo (n = 154)
Serum Creatinine ≥ 2.5 mg/dL | 16% | 10%
Serum Creatinine ≥ 1.5 to < 2.5 mg/dL | 39% | 42%

In 3 out of 4 trials, patients receiving either ganciclovir-IV solution or ganciclovir capsules had elevated serum creatinine levels when compared to those receiving placebo. Most patients in these studies also received cyclosporine. The mechanism of impairment of renal function is not known. However, careful monitoring of renal function during therapy with ganciclovir capsules is essential, especially for those patients receiving concomitant agents that may cause nephrotoxicity.

General

Other adverse events that were thought to be “probably” or “possibly” related to ganciclovir capsules in controlled clinical studies in either subjects with AIDS or transplant recipients are listed below. These events all occurred in at least 3 subjects.

Body as a Whole: abdomen enlarged, asthenia, chest pain, edema, headache, injection site inflammation, malaise, pain

Digestive System: abnormal liver function test, aphthous stomatitis, constipation, dyspepsia, eructation

Hemic and Lymphatic System: pancytopenia

Respiratory System: cough increased, dyspnea

Nervous System: abnormal dreams, anxiety, confusion, depression, dizziness, dry mouth, insomnia, seizures, somnolence, thinking abnormal, tremor

Skin and Appendages: alopecia, dry skin

Special Senses: abnormal vision, taste perversion, tinnitus, vitreous disorder

Metabolic and Nutritional Disorders: creatinine increased, SGOT increased, SGPT increased, weight loss

Cardiovascular System: hypertension, phlebitis, vasodilatation

Urogenital System: creatinine clearance decreased, kidney failure, kidney function abnormal, urinary frequency

Musculoskeletal System: arthralgia, leg cramps, myalgia, myasthenia

The following adverse events reported in patients receiving ganciclovir may be potentially fatal: gastrointestinal perforation, multiple organ failure, pancreatitis and sepsis.

Adverse Events Reported During Postmarketing Experience With Ganciclovir Capsules

The following events have been identified during postapproval use of the drug. Because they are reported voluntarily from a population of unknown size, estimates of frequency cannot be made. These events have been chosen for inclusion due to either the seriousness, frequency of reporting, the apparent causal connection or a combination of these factors:

acidosis, allergic reaction, anaphylactic reaction, arthritis, bronchospasm, cardiac arrest, cardiac conduction abnormality, cataracts, cholelithiasis, cholestasis, congenital anomaly, dry eyes, dysesthesia, dysphasia, elevated triglyceride levels, encephalopathy, exfoliative dermatitis, extrapyramidal reaction, facial palsy, hallucinations, hemolytic anemia, hemolytic uremic syndrome, hepatic failure, hepatitis, hypercalcemia, hyponatremia, inappropriate serum ADH, infertility, intestinal ulceration, intracranial hypertension, irritability, loss of memory, loss of sense of smell, myelopathy, oculomotor nerve paralysis, peripheral ischemia, pulmonary fibrosis, renal tubular disorder, rhabdomyolysis, Stevens-Johnson syndrome, stroke, testicular hypotrophy, Torsades de Pointes, vasculitis, ventricular tachycardia

OVERDOSAGE

There have been no reports of overdosage with ganciclovir capsules. Doses as high as 6000 mg/day, given either as 1000 mg 6 times daily or as 2000 mg tid, did not result in overt toxicity other than transient neutropenia. Daily doses of more than 6000 mg have not been studied.

Since ganciclovir is dialyzable, dialysis may be useful in reducing serum concentrations. Adequate hydration should be maintained. The use of hematopoietic growth factors should be considered.

DOSAGE AND ADMINISTRATION

Dosage: THE RECOMMENDED DOSE FOR GANCICLOVIR CAPSULES SHOULD NOT BE EXCEEDED.

For Treatment of CMV Retinitis in Patients With Normal Renal Function:

1. Induction Treatmen t

Ganciclovir capsules should not be used for induction treatment.

2. Maintenance Treatment

Following induction treatment, the recommended maintenance dosage of ganciclovir capsules is 1000 mg tid with food. Alternatively, the dosing regimen of 500 mg 6 times daily every 3 hours with food, during waking hours, may be used.

For patients who experience progression of CMV retinitis while receiving maintenance treatment with either formulation of ganciclovir, reinduction treatment is recommended.

For the Prevention of CMV Disease in Patients With Advanced HIV Infection and Normal Renal Function:

The recommended prophylactic dose of ganciclovir capsules is 1000 mg tid with food.

For the Prevention of CMV Disease in Transplant Recipients With Normal Renal Function:

The recommended prophylactic dosage of ganciclovir capsules is 1000 mg tid with food.

The duration of treatment with ganciclovir capsules in transplant recipients is dependent upon the duration and degree of immunosuppression. In a controlled clinical trial of liver allograft recipients, treatment with ganciclovir capsules was continued through week 14 posttransplantation (see INDICATIONS AND USAGE section for a more detailed discussion).

Renal Impairment:

In patients with renal impairment, the dose of ganciclovir capsules should be modified as shown below:

Creatinine Clearance*
mL/min | Ganciclovir capsule Doses
≥ 70 | 1000 mg tid | or | 500 mg q3h, 6x/day
50 to 69 | 1500 mg qd | or | 500 mg tid
25 to 49 | 1000 mg qd | or | 500 mg bid
10 to 24 | 500 mg qd
< 10 | 500 mg 3 times per week, following hemodialysis
*Creatinine clearance can be related to serum creatinine by the following formulas:

Creatinine clearance for males = | (140 - age [yrs]) (body wt [kg])
Creatinine clearance for males = | (72) (serum creatinine [mg/dL]

Creatinine clearance for females = 0.85 x male value

Patient Monitoring: Due to the frequency of granulocytopenia, anemia and thrombocytopenia in patients receiving ganciclovir (see ADVERSE EVENTS), it is recommended that complete blood counts and platelet counts be performed frequently, especially in patients in whom ganciclovir or other nucleoside analogues have previously resulted in cytopenia, or in whom neutrophil counts are less than 1000 cells/µL at the beginning of treatment. Patients should have serum creatinine or creatinine clearance values followed carefully to allow for dosage adjustments in renally impaired patients (see DOSAGE AND ADMINISTRATION).

Reduction of Dose: Dosage reductions in renally impaired patients should be considered for ganciclovir capsules (see Renal Impairment). Dosage reductions should also be considered for those with neutropenia, anemia and/or thrombocytopenia (see ADVERSE EVENTS). Ganciclovir should not be administered in patients with severe neutropenia (ANC less than 500/µL) or severe thrombocytopenia (platelets less than 25,000/µL).

Handling and Disposal: Caution should be exercised in the handling of ganciclovir capsules. Avoid direct contact with the skin or mucous membranes of the powder contained in ganciclovir capsules. If such contact occurs, wash thoroughly with soap and water; rinse eyes thoroughly with plain water. Ganciclovir capsules should not be opened or crushed.

Because ganciclovir shares some of the properties of antitumor agents (ie, carcinogenicity and mutagenicity), consideration should be given to handling and disposal according to guidelines issued for antineoplastic drugs. Several guidelines on this subject have been published.

There is no general agreement that all of the procedures recommended in the guidelines are necessary or appropriate.

HOW SUPPLIED

Ganciclovir 250 mg capsules are opaque green cap/opaque green body; size ‘1’ hard gelatin capsules, printed “RX636” on cap and body in black ink, containing white to off-white granular powder. They are supplied as follows:

NDC 63304-636-60 Bottles of 60

NDC 63304-636-90 Bottles of 90

NDC 63304-636-28 Bottles of 180

NDC 63304-636-10 Bottles of 1000

Ganciclovir 500 mg capsules are opaque ivory yellow cap/opaque green body, size ‘0’ elongated hard gelatin capsules, printed “RX637” on cap and body in black ink, containing white to off-white granular powder. They are supplied as follows:

NDC 63304-637-60 Bottles of 60

NDC 63304-637-90 Bottles of 90

NDC 63304-637-28 Bottles of 180

NDC 63304-637-05 Bottles of 500

Store at 20 - 25° C (68 - 77° F) [See USP Controlled Room Temperature].

Call your doctor for medical advice about side effects. You may report side effects to FDA at 1-800-FDA-1088.

* Retrovir® is a registered trademark of Glaxo Wellcome.

# Videx® is a registered trademark of Bristol-Myers Squibb.

REFERENCES

1. Drew WL, Ives D, Lalezari JP, et al. Oral ganciclovir as maintenance treatment for cytomegalovirus retinitis in patients with AIDS. New Engl J Med. 1995; 333:615-620.

2. The Oral Ganciclovir European and Australian Cooperative Study Group. Intravenous vs oral ganciclovir: European/Australian comparative study of efficacy and safety in the prevention of cytomegalovirus retinitis recurrence in patients with AIDS. AIDS. 1995; 9:471-477.

3. Spector SA, McKinley GF, Lalezari JP, Samo T, et al. Oral ganciclovir for the prevention of cytomegalovirus disease in persons with AIDS. New Engl J Med. 1996; 334:1491-1497.

Manufactured for:

Ranbaxy Pharmaceuticals Inc.

Jacksonville, FL 32257 USA

by: Ranbaxy Laboratories Ltd.

New Delhi – 110 019, India

March 2009

PACKAGE LABEL.PRINCIPAL DISPLAY PANEL

250 mg 90's Label
500 mg 90's Label